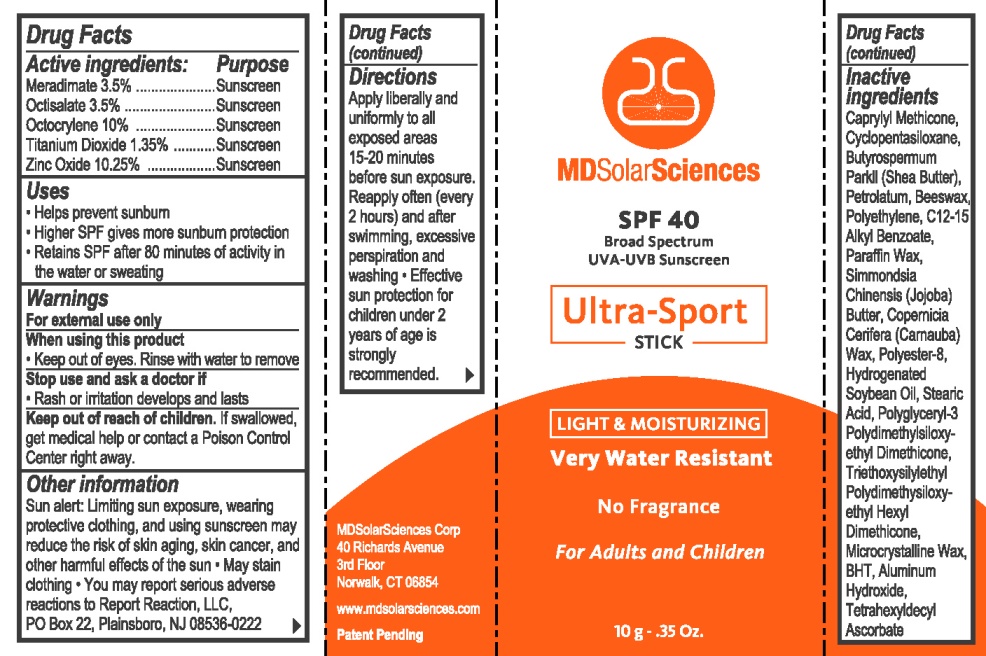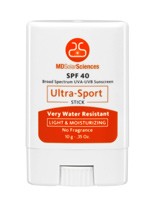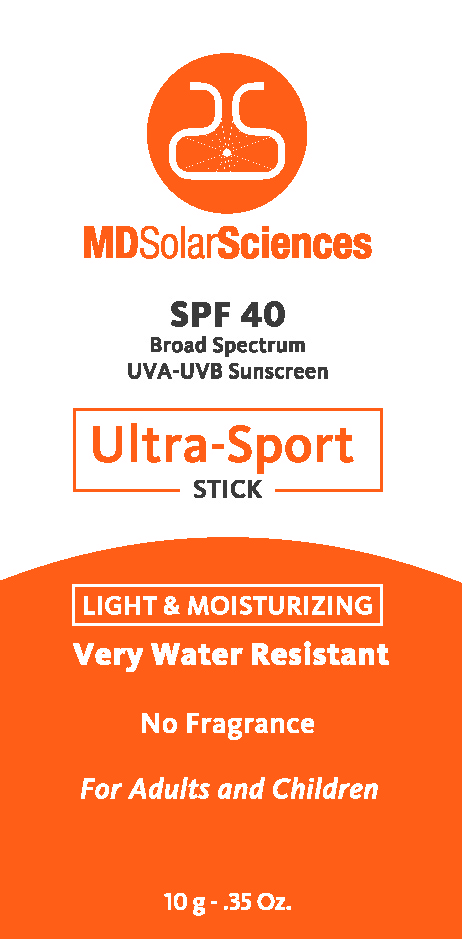 DRUG LABEL: MDSolarSciences SPF40 Ultra-Sport
NDC: 17452-360 | Form: STICK
Manufacturer: Ecometics, Inc
Category: otc | Type: HUMAN OTC DRUG LABEL
Date: 20101015

ACTIVE INGREDIENTS: Meradimate 0.35 g/10 g; Octisalate 0.35 g/10 g; Octocrylene 1 g/10 g; Titanium Dioxide 0.135 g/10 g; Zinc Oxide 1.025 g/10 g
INACTIVE INGREDIENTS: SHEA BUTTER; PETROLATUM; YELLOW WAX; C12-15 ALKYL BENZOATE; JOJOBA OIL; Carnauba Wax; POLYESTER-8 (1400 MW, CYANODIPHENYLPROPENOYL CAPPED); BUTYLATED HYDROXYTOLUENE; TETRAHEXYLDECYL ASCORBATE

Drug Facts

Active Igredients

Meradimate 3.50% .......... Sunscreen

Octisalate 3.50% .......... Sunscreen

Octocrylene 10.00% .......... Sunscreen

Titanium Dioxide 1.35% .......... Sunscreen

Zinc Oxide 10.25% .......... Sunscreen

Uses

Helps prevent sunburn

Higher SPF gives more sunburn protection

Retains SPF after 80 minutes of activity in the water or sweating

Warnings

For external uses only.

When using this product
keep out of eyes. Rinse with water to remove.

Stop use and ask a doctor if
rash or irritation develops and lasts.

Keep out of reach of children.
If swallowed,
get medical help or contact a Poison Control
Center right away

Other Information

Sun alert: Limiting sun exposure, wearing
protective clothing, and using sunscreen may
reduce the risk of skin aging, skin cancer, and
other harmful effects of the sun.
May stain
clothing.You may report serious adverse
reactions to Report Reactions, LLC,
PO Box 22, Plainsboro, NJ 08536-0222

Inactive Ingredients

Caprlyl Methicone, Cyclopentasiloxane, Butyrospemum Parkll (Shea Butter), Petrolatum, Beesewax, Polyethylene, C12-15 Alkyl Benzoate, Paraffin Wax, Simmondsia Chinensis (Jojoba) Butter, Copernicia Cerifera (Carnauba) Wax, Polyester-8, Hydrogenated Soybean Oil, Stearic Acid, Polyglyceryl-3 Polydimethylsiloxyethyl Dimethicone, Triethoxysilylethyl Polydimethysiloxyethyl Hexyl Dimethicone, Microcrystalline Wax, BHT, Aluminum Hydroxide, Tetrahexyldecyl Ascorbate

Directions

Apply liberally and uniformly to all exposed areas 15-20 minutes before sun exposure. Reapply often (every 2 hours) and after swimming, excessive perspiration and washing. Effective sun protection for children under 2 years of age is strongly recommended.

Principle Display Panel

MDSolarSciences
SPF 40
Broad Spectrum
UVA-UVB Sunscreen
Ultra-Sport
Stick
LIGHT and MOISTURIZING
Very Water Resistant
No Fragrance
For Adults and Children
10 g - .35 Oz

Additional Carton Labeling

MDSolarSciences Corp
40 Richards Avenue, 3rd Floor, Norwalk, CT 06854
www.mdsolarsciences.com
Patent Pending
UPC 8 55488 00204 2